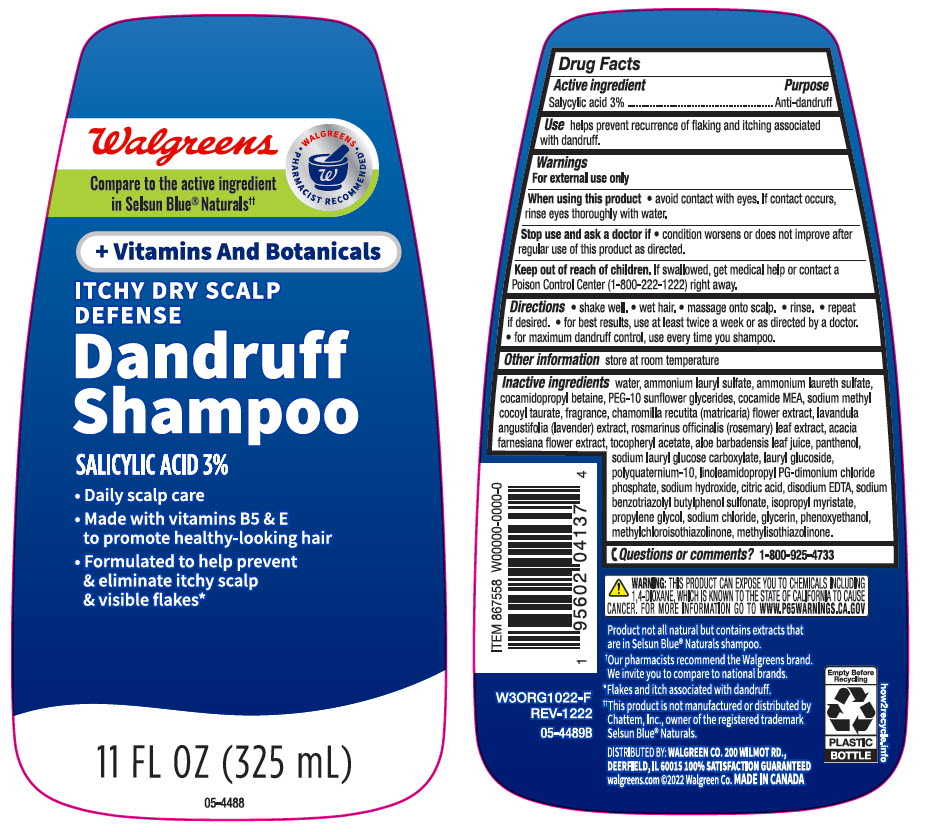 DRUG LABEL: Walgreens Dandruff Itchy Dry Scalp Defense Plus Vitamins and Botanicals
NDC: 0363-4137 | Form: SHAMPOO
Manufacturer: Walgreen Company
Category: otc | Type: HUMAN OTC DRUG LABEL
Date: 20241101

ACTIVE INGREDIENTS: Salicylic Acid 30 mg/1 mL
INACTIVE INGREDIENTS: Water; Ammonium Lauryl Sulfate; COCAMIDOPROPYL BETAINE; COCO MONOETHANOLAMIDE; Sodium Methyl Cocoyl Taurate; CHAMOMILE; LAVANDULA ANGUSTIFOLIA SUBSP. ANGUSTIFOLIA FLOWERING TOP; ROSEMARY; VACHELLIA FARNESIANA FLOWER; .ALPHA.-TOCOPHEROL ACETATE, DL-; ALOE VERA LEAF; Panthenol; Lauryl Glucoside; POLYQUATERNIUM-10 (30000 MPA.S AT 2%); LINOLEAMIDOPROPYL PROPYLENE GLYCOL-DIMONIUM CHLORIDE PHOSPHATE; Sodium Hydroxide; CITRIC ACID MONOHYDRATE; EDETATE DISODIUM; SODIUM BENZOTRIAZOLYL BUTYLPHENOL SULFONATE; Isopropyl Myristate; Propylene Glycol; Sodium Chloride; Glycerin; Phenoxyethanol; Methylchloroisothiazolinone; Methylisothiazolinone

Walgreens Dandruff Shampoo Itchy Dry Scalp Defense + Vitamins and Botanicals
Anti-dandruff

Drug Facts

Active ingredient

Salicylic Acid 3%

Purpose

Anti-dandruff

Use

helps prevent recurrence of flaking and itching associated with dandruff.

Warnings

For external use only

When using this product

- avoid contact with the eyes. If contact occurs, rinse eyes thoroughly with water.

Stop use and ask a doctor if

- condition worsens or does not improve after regular use as directed.

Keep out of reach of children. If swallowed, get medical help or contact a Poison Control Center (1-800-222-1222) right away.

Directions

- shake well
- wet hair
- massage onto scalp
- rinse
- repeat if desired
- for best results use at least twice a week or as directed by a doctor
- for maximum dandruff control, use every time you shampoo.

Other information

store at room temperature

Inactive ingredients

water, ammonium lauryl sulfate, ammonium laureth sulfate, cocamidopropyl betaine, PEG-10 sunflower glycerides, cocamide MEA, sodium methyl cocoyl taurate, fragrance, chamomilla recutita (matricaria) flower extract, lavandula angustifola (lavender) extract, rosmarinus officinalis (rosemary) leaf extract, acacia farnesiana flower extract, tocopheryl acetate, aloe barbadensis leaf juice, panthenol, sodium lauryl glucose carboxylate, lauryl glucoside, polyquaternium-10, linoleamidopropyl PG-dimonium chloride phosphate, sodium hydroxide, citric acid, disodium EDTA, sodium benzotriazolyl butylphenol sulfonate, isopropyl myristate, propylene glycol, sodium chloride, glycerin, phenoxyethanol, methylchloroisothiazolinone, methylisothiazolinone.

Questions or Comments?

1-800-925-4733

DISTRIBUTED BY: WALGREEN CO. 200 WILMOT RD.,
DEERFIELD, IL 60015

PRINCIPAL DISPLAY PANEL - 325 mL Bottle Label

Walgreens

• WALGREENS •
PHARMACIST RECOMMENDED†

Compare to the active ingredient
in Selsun Blue® Naturals††

+ Vitamins And Botanicals

ITCHY DRY SCALP
DEFENSE

Dandruff
Shampoo

SALICYLIC ACID 3%

- Daily scalp care
- Made with vitamins B5 & E
  to promote healthy-looking hair
- Formulated to help prevent
  & eliminate itchy scalp
  & visible flakes*

11 FL OZ (325 mL)

05-4488